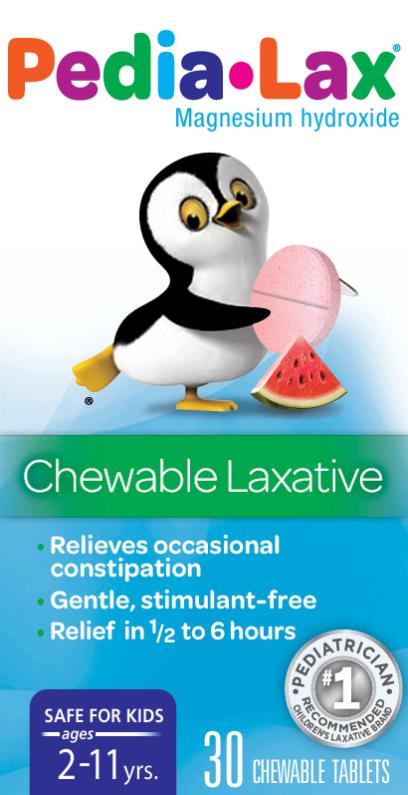 DRUG LABEL: Pedia-Lax
NDC: 0132-0655 | Form: TABLET, CHEWABLE
Manufacturer: C.B. Fleet Company, Inc.
Category: otc | Type: HUMAN OTC DRUG LABEL
Date: 20240411

ACTIVE INGREDIENTS: MAGNESIUM HYDROXIDE 400 mg/1 1
INACTIVE INGREDIENTS: SILICON DIOXIDE; FD&C RED NO. 40; MAGNESIUM STEARATE; MALTODEXTRIN; MANNITOL; SORBITOL; STEARIC ACID; SUCRALOSE

Pedia-Lax Chewable Tablets 0132-0655-01

Pedia-Lax Chewable Tablets

Drug Facts

Active Ingredient (in each tablet)

Magnesium hydroxide 400 mg

Purpose

Saline laxative

Uses

- For relief of occasional constipation
- This product usually produces abowel movement in 1/2 to 6 hours

Ask a doctor before using any laxative if child has

- kidney disease
- a magnesium-restricted diet
- abdominal pain, nausea or vomiting
- a sudden change in bowel habits lasting more than 2 weeks
- constipation that continues after 1 week of use, contact your child's doctor
- already used a laxative for more than 1 week

Stop using this product and consult a doctor if your child

- has rectal bleeding
- does not have a bowel movement within 6 hours of using this product
- these symptoms maybe signs of a serious condition

Keep out of reach of children.

In case of overdose, get medical help or contact Poison Control Center (1-800-222-1222) right away.

Directions

Use dosage chart for proper dosing. Doses may be taken as a single daily dose or in divided doses. Drink a full glass (8 ounces) of liquid with each dose.

Age | Starting dose | Starting Dose Maximum dose per day (24 hours)
children 6 to under 12 years | 3-6 tablets | 6 tablets
children 2 to under 6 years | 1-3 tablets | 3 tablets
children under 2 years | ask a doctor

Other information

- each tablet contains : 170 mg of magnesium
- CHILD RESISTANT CAP
- The top of the bottle sealed for safety. Do not use if foil imprinted "SEALED for YOUR PROTECTION" is broken of missing.
- Gluten Free and Sugar Free

Inactive ingredients

colloidal silicon dioxide, FD&C red #40 aluminum lake, flavor, magnesium stearate, maltodextrin, mannitol, sorbitol, stearic acid, sucralose

Questions?

1-866-255-6960 or www.pedia-lax.com

PRINCIPAL DISPLAY PANEL

Pedia-Lax®
Magnesium hydroxide
Chewable Laxative
30 chewable tablets